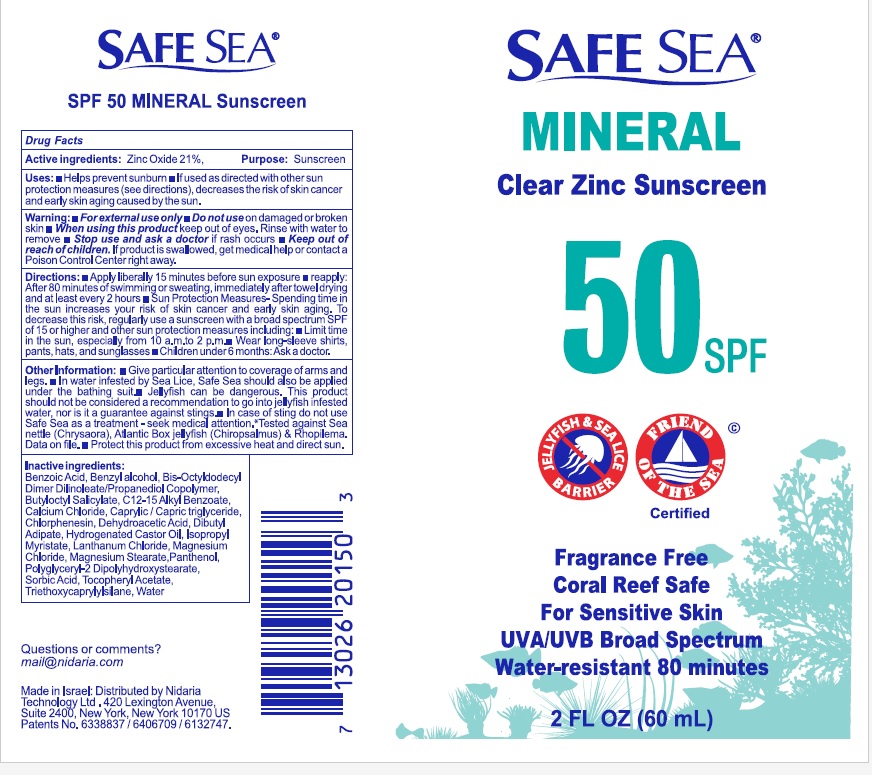 DRUG LABEL: Safe Sea SPF 50 Mineral
NDC: 65435-0400 | Form: LOTION
Manufacturer: Nidaria Technology Ltd.
Category: otc | Type: HUMAN OTC DRUG LABEL
Date: 20251124

ACTIVE INGREDIENTS: ZINC OXIDE 210 mg/1 mL
INACTIVE INGREDIENTS: PANTHENOL; .ALPHA.-TOCOPHEROL ACETATE; LANTHANUM CHLORIDE; MAGNESIUM CHLORIDE; CALCIUM CHLORIDE; BENZYL ALCOHOL; CHLORPHENESIN; BENZOIC ACID; SORBIC ACID; DEHYDROACETIC ACID; WATER; ALKYL (C12-15) BENZOATE; MEDIUM-CHAIN TRIGLYCERIDES; DIBUTYL ADIPATE; BUTYLOCTYL SALICYLATE; POLYGLYCERYL-2 DIPOLYHYDROXYSTEARATE; ISOPROPYL MYRISTATE; BIS-OCTYLDODECYL DIMER DILINOLEATE/PROPANEDIOL COPOLYMER; TRIETHOXYCAPRYLYLSILANE; MAGNESIUM STEARATE; HYDROGENATED CASTOR OIL

Drug Facts

Active ingredient

Zinc oxide 21%

Purpose

Sunscreen

Other information

- Give perticular attention to coverage of arms and legs.
- In water infested by sea Lice, safe sea should also be applied under the bathing suit.
- Jellyfish can be dangerous. This product should be considered a recommendation to go into jellyfish infested water, nor is it guarantee against stings.
- In case of stings do not use Safe sea as a treatement - seek medical attention. *Tested against sea nettle (Chrysaora), Atlantic box jellyfish (Chiropsalmus) & Rhopilema.Data on file.
- Protect this product from excessive heat and direact sun.

Warnings

- For external use only.
- Do not use on damaged or broken skin.
- When using this product keep out of eyes. Rinse with water to remove.
- Stop use and ask a doctor if rash occurs.
- Keep out of reach of children. If product is swallowed, get medical help or contact a Poison Control Center right away.

Directions

- Apply liberally 15 minutes before sun exposure
- reapply: after 80 minutes of swimming or sweating, immediately after towel drying and at least every 2 hours
- Sun protection Measure- Spending time in the sun increase your skin cancer and early skin aging.To decrease this risk, regularly use a sunscreen with a broad spectrum SPF of 15 or higher and other sun protection measures including: limit time in the sun, especially from 10a.m. to 2 p.m.
- Wear long-sleeve shirts, pants, hats, and sunglasses
- Children under 6 months : Ask a doctor

Uses

- Helps prevent sunburn
- If used as direacted with other sun protection measures (see directions), decreases the risk of skin cancer and early aging skin caused by the sun

Inactive ingredients

Benzoic acid, Benzyl alcohol, Bis-Octyldodecyl, Dimer Dilinoleate/ Propanediol copolymer, Butyloctyl Salicylate, C12 -15 Alkyl benzoate, Calcium chloride, Caprylic / Capric triglyceride, Chlorphenesin, Dehydroacetic acid, Dibutyl Adipate, Hydrogenated Caster oil, Isopropyl Myristate, Lanthanum chloride, Magnesium Chloride, Magnesium stearate, Panthenol, Polyglycerly-2Dipolyhydroxystearate, Sorbic acid, Tocopheryl Acetate, Triethoxycaprylylsilane, water.